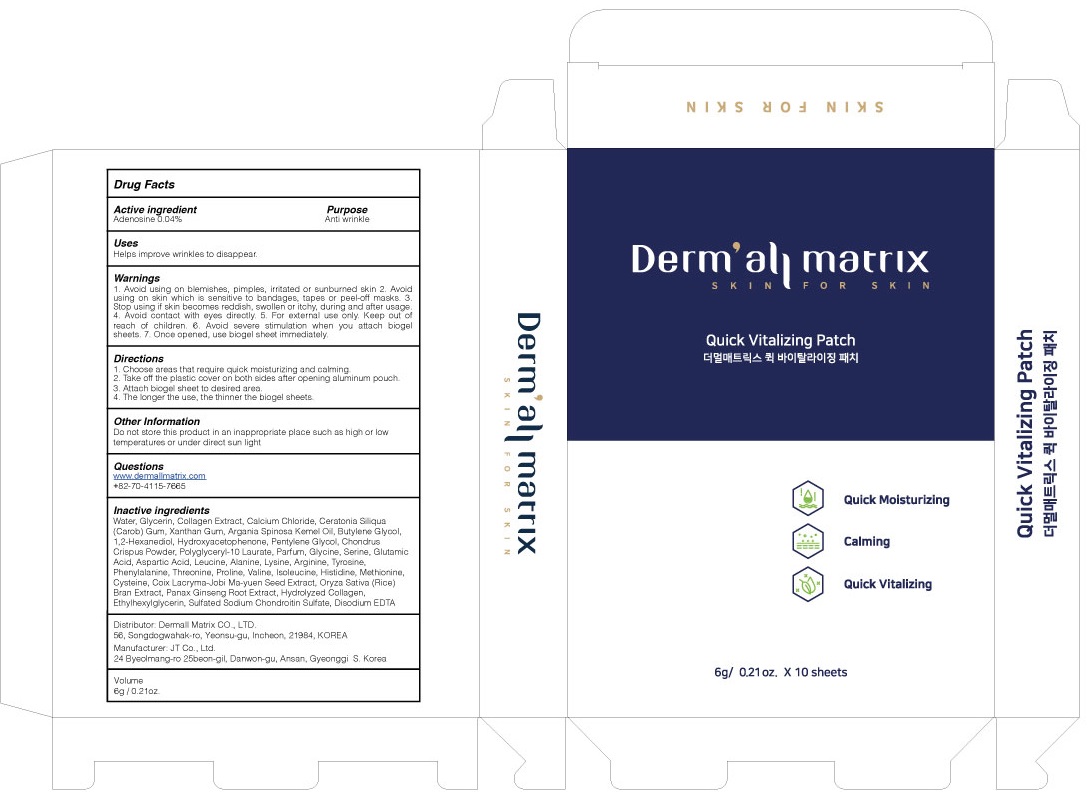 DRUG LABEL: Dermall Matrix Quick Vitalizing
NDC: 82428-010 | Form: PATCH
Manufacturer: Dermall Matrix Co., Ltd.
Category: otc | Type: HUMAN OTC DRUG LABEL
Date: 20211215

ACTIVE INGREDIENTS: Adenosine 0.04 g/100 g
INACTIVE INGREDIENTS: Water; Glycerin; Calcium Chloride

ACTIVE INGREDIENT

Adenosine 0.04%

INACTIVE INGREDIENTS

Water, Glycerin, Collagen Extract, Calcium Chloride, Ceratonia Siliqua (Carob) Gum, Xanthan Gum, Argania Spinosa Kemel Oil, Butylene Glycol, 1,2-Hexanediol, Hydroxyacetophenone, Pentylene Glycol, Chondrus Crispus Powder, Polyglyceryl-10 Laurate, Parfum, Glycine, Serine, Glutamic Acid, Aspartic Acid, Leucine, Alanine, Lysine, Arginine, Tyrosine, Phenylalanine, Threonine, Proline, Valine, Isoleucine, Histidine, Methionine, Cysteine, Coix Lacryma-Jobi Ma-yuen Seed Extract, Oryza Sativa (Rice) Bran Extract, Panax Ginseng Root Extract, Hydrolyzed Collagen, Ethylhexylglycerin, Sulfated Sodium Chondroitin Sulfate, Disodium EDTA

PURPOSE

Anti wrinkle

WARNINGS

1. Avoid using on blemishes, pimples, irritated or sunburned skin 2. Avoid using on skin which is sensitive to bandages, tapes or peel-off masks. 3. Stop using if skin becomes reddish, swollen or itchy, during and after usage. 4. Avoid contact with eyes directly. 5. For external use only. Keep out of reach of children. 6. Avoid severe stimulation when you attach biogel sheets. 7. Once opened, use biogel sheet immediately.

KEEP OUT OF REACH OF CHILDREN

Uses

Helps improve wrinkles to disappear.

Directions

1. Choose areas that require quick moisturizing and calming.
2. Take off the plastic cover on both sides after opening aluminum pouch.
3. Attach biogel sheet to desired area.
4. The longer the use, the thinner the biogel sheets.

Other Information

Do not store this product in an inappropriate place such as high or low temperatures or under direct sun light

Questions

www.dermallmatrix.com
+82-70-4115-7665